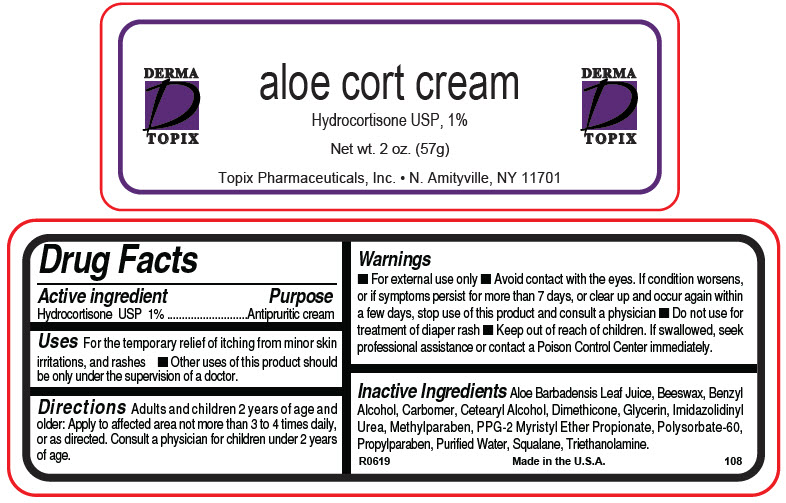 DRUG LABEL: Aloe Cort
NDC: 51326-108 | Form: CREAM
Manufacturer: Topiderm, Inc.
Category: otc | Type: HUMAN OTC DRUG LABEL
Date: 20190917

ACTIVE INGREDIENTS: HYDROCORTISONE 0.57 g/57 g
INACTIVE INGREDIENTS: ALOE; YELLOW WAX; BENZYL ALCOHOL; CETOSTEARYL ALCOHOL; CARBOMER HOMOPOLYMER, UNSPECIFIED TYPE; GLYCERIN; IMIDUREA; METHYLPARABEN; PPG-2 MYRISTYL ETHER PROPIONATE; POLYSORBATE 60; PROPYLPARABEN; WATER; SQUALANE; TROLAMINE; DIMETHICONE

Aloe Cort Cream

Drug Facts

Active ingredient

Hydrocortisone USP 1%

Purpose

Antipruritic cream

Uses

For the temporary relief of itching from minor skin irritations, and rashes

- Other uses of this product should be only under the supervision of a doctor.

Directions

Adults and children 2 years of age and older: Apply to affected area not more than 3 to 4 times daily, or as directed. Consult a physician for children under 2 years of age.

Warnings

- For external use only
- Avoid contact with the eyes. If condition worsens, or if symptoms persist for more than 7 days, or clear up and occur again within a few days, stop use of this product and consult a physician
- Do not use for treatment of diaper rash

- Keep out of reach of children. If swallowed, seek professional assistance or contact a Poison Control Center immediately.

Inactive Ingredients

Aloe Barbadensis Leaf Juice, Beeswax, Benzyl Alcohol, Carbomer, Cetearyl Alcohol, Dimethicone, Glycerin, Imidazolidinyl Urea, Methylparaben, PPG-2 Myristyl Ether Propionate, Polysorbate-60, Propylparaben, Purified Water, Squalane, Triethanolamine.

PRINCIPAL DISPLAY PANEL - 57 g Tube Label

DERMA
TOPIX

aloe cort cream

Hydrocortisone USP, 1%

Net wt. 2 oz. (57g)

Topix Pharmaceuticals, Inc. • N. Amityville, NY 11701

DERMA
TOPIX